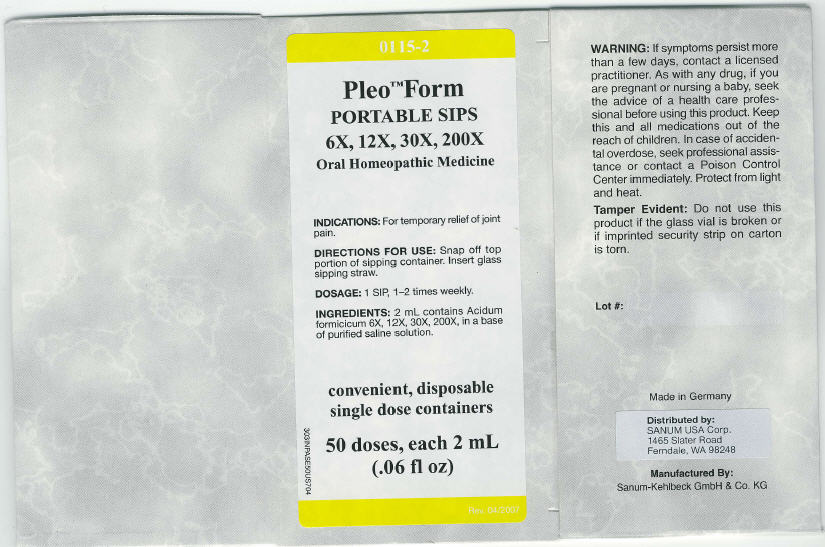 DRUG LABEL: Pleo Form
NDC: 60681-0115 | Form: KIT | Route: ORAL
Manufacturer: Sanum Kehlbeck GmbH & Co. KG
Category: homeopathic | Type: HUMAN OTC DRUG LABEL
Date: 20091120

ACTIVE INGREDIENTS: formic acid 6 [hp_X]/2 mL; formic acid 12 [hp_X]/2 mL; formic acid 30 [hp_X]/2 mL; formic acid 200 [hp_X]/2 mL
INACTIVE INGREDIENTS: water; sodium chloride; water; sodium chloride; water; sodium chloride; water; sodium chloride

Pleo™ Form
PORTABLE SIPS
6X, 12X, 30X, 200X

Oral Homeopathic Medicine

50 doses, each 2 mL
(.06 fl oz)

INDICATIONS

For temporary relief of joint pain.

DIRECTIONS FOR USE

Snap off top portion of sipping container. Insert glass sipping straw.

DOSAGE

1 SIP, 1–2 times weekly.

INGREDIENTS

2 mL contains Acidum formicicum 6X, 12X, 30X, 200X, in a base of purified saline solution.

WARNING

If symptoms persist more than a few days, contact a licensed practitioner. As with any drug, if you are pregnant or nursing a baby, seek the advice of a health care professional before using this product.

KEEP OUT OF REACH OF CHILDREN

Keep this and all medications out of the reach of children. In case of accidental overdose, seek professional assistance or contact a Poison Control Center immediately.

STORAGE AND HANDLING

Protect from light and heat.

Tamper Evident

Do not use this product if the glass vial is broken or if imprinted security strip on carton is torn.

Made in Germany

Distributed by:
SANUM USA Corp.
1465 Slater Road
Ferndale, WA 98248

Manufactured By:
Sanum-Kehlbeck GmbH & Co. KG

Rev. 04/2007

PRINCIPAL DISPLAY PANEL - 2 mL Carton

0115-2

Pleo™ Form
PORTABLE SIPS
6X, 12X, 30X, 200X

Oral Homeopathic Medicine

INDICATIONS: For temporary relief of joint
pain.

DIRECTIONS FOR USE: Snap off top
portion of sipping container. Insert glass
sipping straw.

DOSAGE: 1 SIP, 1–2 times weekly.

INGREDIENTS: 2 mL contains Acidum
formicicum 6X, 12X, 30X, 200X, in a base
of purified saline solution.

convenient, disposable
single dose containers

50 doses, each 2 mL
(.06 fl oz)

Rev. 04/2007
303INPASE50US704